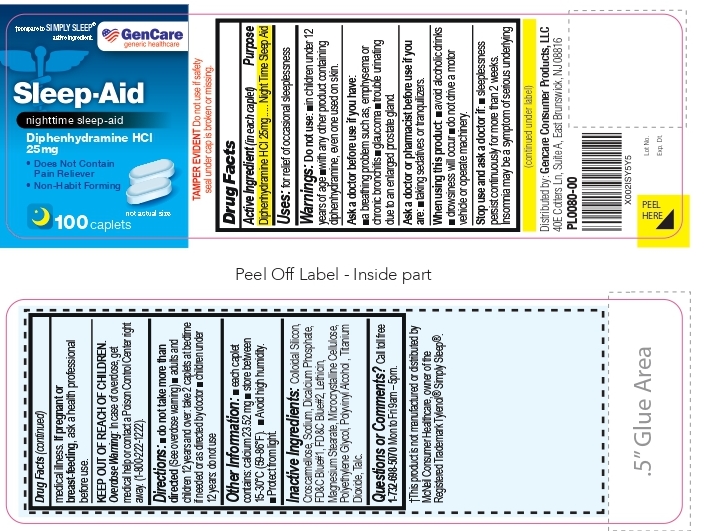 DRUG LABEL: Sleep Aid
NDC: 72090-020 | Form: TABLET
Manufacturer: Pioneer Life Sciences, LLC
Category: otc | Type: HUMAN OTC DRUG LABEL
Date: 20251229

ACTIVE INGREDIENTS: DIPHENHYDRAMINE HYDROCHLORIDE 25 mg/1 1
INACTIVE INGREDIENTS: SILICON DIOXIDE; CROSCARMELLOSE SODIUM; ANHYDROUS DIBASIC CALCIUM PHOSPHATE; FD&C BLUE NO. 1; FD&C BLUE NO. 2; LECITHIN, SOYBEAN; MAGNESIUM STEARATE; MICROCRYSTALLINE CELLULOSE; POLYETHYLENE GLYCOL, UNSPECIFIED; TITANIUM DIOXIDE; TALC

Nighttime Sleep Aid

Active Ingredient (in each caplet)

Diphenhydramine HCl 25mg

Purpose

Night Time Sleep Aid

Uses:

for relief of occasional sleeplessness

Warnings:

Do not use:

■ in children under 12 years of age ■with any other product containing diphenhydramine, even one used on skin.

Ask a doctor before use if you have:

■ a breathing problem such as, emphysema or chronic bronchitis

■ glaucoma

■ trouble urinating due to an enlarged prostate gland.

Ask a doctor or pharmacist before use if you are:■taking sedatives or tranquilizers.

When using this product:

■ avoid alcoholic drinks
■ drowsiness will occur

■ do not drive a motorvehicle or operate machinery.

Stop use and ask a doctor if:

■ sleeplessness persist continuously for more than 2 weeks. Insomnia may be a symptom of serious underlying medical illness.

PREGNANCY OR BREAST FEEDING

If pregnant or breast-feeding,ask a health professional before use.

KEEP OUT OF REACH OF CHILDREN

Overdose Warning:In case of overdose, get medical help or contact a Poison Control Center right away. (1-800-222-1222).

DIRECTIONS

■ do not take more than directed(See overdose warning)

■ adults and children 12 years and over: take 2 caplets at bedtime if needed or as directed by doctor

■ children under 12 years: do not use

OTHER INFORMATION

■each caplet contains: calcium 23.52 mg

■store between 15-30°C (59-86°F).

■Avoid high humidity.

■ Protect from light.

INACTIVE INGREDIENTS

Colloidal Silicon, Croscarmellose, Sodium, Dicalcium Phosphate, FD&C Blue#1, FD&C Blue#2, Lethicin, Magnesium Stearate, Microcrystalline Cellulose, Polyethylene Glycol, Polyvinyl Alcohol , Titanium Dioxide, Talc.

QUESTIONS OR COMMENTS?

Call toll free 1-732-698-5070 Mon to Fri 9am – 5pm.